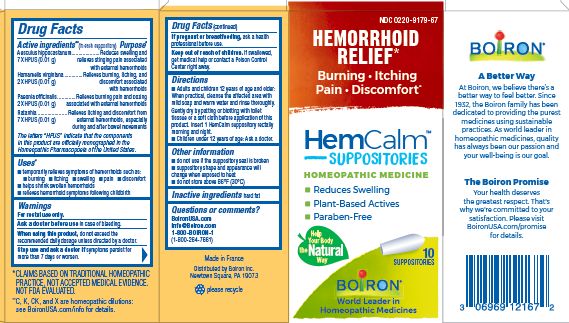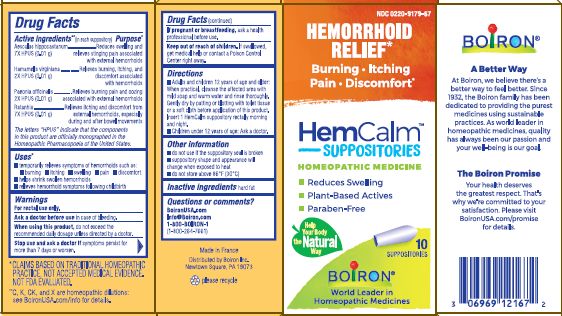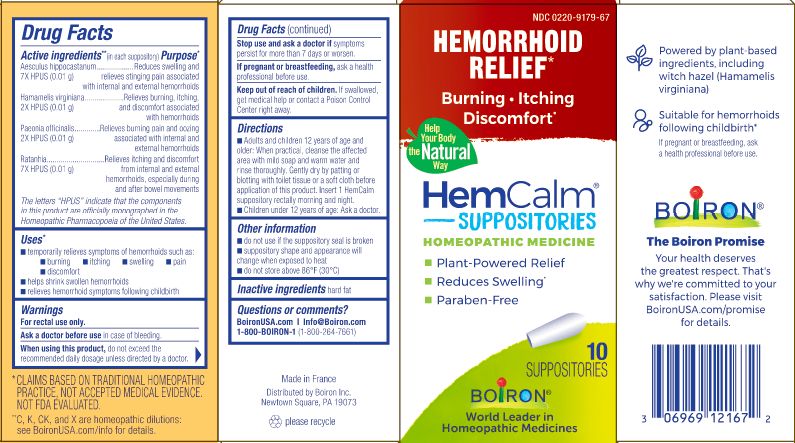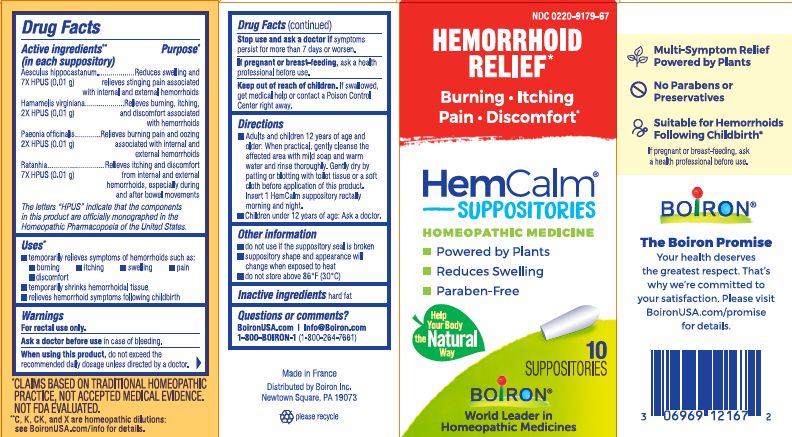 DRUG LABEL: HemCalm
NDC: 0220-9179 | Form: SUPPOSITORY
Manufacturer: Boiron
Category: homeopathic | Type: HUMAN OTC DRUG LABEL
Date: 20240214

ACTIVE INGREDIENTS: PAEONIA OFFICINALIS ROOT 2 [hp_X]/1 1; HORSE CHESTNUT 7 [hp_X]/1 1; HAMAMELIS VIRGINIANA ROOT BARK/STEM BARK 2 [hp_X]/1 1; KRAMERIA LAPPACEA ROOT 7 [hp_X]/1 1
INACTIVE INGREDIENTS: HARD FAT

HEMCALM SUPPOSITORIES

Active Ingredients** (in each suppository)

Aesculus hippocastanum 7X HPUS (0.01 g)

Hamamelis virginiana 2X HPUS (0.01 g)

Paeonia officinalis 2X HPUS (0.01 g)

Ratanhia 7X HPUS (0.01 g)

The letters "HPUS" indicate that the components in this product are officially monographed in the Homeopathic Pharmacopoeia of the United States.

Purpose*

Aesculus hippocastanum 7X HPUS (0.01g) ... Reduces swelling and relieves stinging pain associated with internal and external hemorrhoids

Hamamelis virginiana 2X HPUS (0.01g) ... Relieves burning, itching and discomfort associated with hemorrhoids

Paeonia officinalis 2X HPUS (0.01g) ... Relieves burning pain and oozing associated with internal and external hemorrhoids

Ratanhia 7X HPUS (0.01g) ... Relieves itching and discomfort from internal and external hemorrhoids, especially during and after bowel movements

Uses*

temporarily relieves symptoms of hemorrhoids such as

- burning
- itching
- swelling
- pain
- discomfort
- helps shrink swollen hemorrhoids
- relieves hemorrhoid symptoms following childbirth

WARNINGS

For rectal use only.

Ask a doctor before use in case of bleeding.

When using this product, do not exceed the recommended daily dosage unless directed by a doctor.

Stop use and ask a doctor if symptoms persist for more than 7 days or worsen.

PREGNANCY OR BREAST FEEDING

If pregnant or breastfeeding, ask a health professional before use.

Keep out of reach of children. If swallowed, get medical help or contact a Poison Control Center right away.

Directions

- Adults and children 12 years of age and older: When practical, cleanse the affected area with mild soap and warm water and rinse thoroughly. Gently dry by patting or blotting with toilet tissue or a soft cloth before application of this product. Insert 1 HemCalm suppository rectally morning and night.
- Children under 12 years of age: Ask a doctor.

Other information

- do not use if the suppository seal is broken
- suppository shape and appearance will change when exposed to heat
- do not store above 86° F (30° C)

10 Suppositories

Hemorrhoid Relief*

Burning Itching Pain Discomfort*

Plant Powered Relief

Reduces Swelling

Paraben-Free

*CLAIMS BASED ON TRADITIONAL HOMEOPATHIC PRACTICE NOT ACCEPTED MEDICAL EVIDENCE. NOT FDA EVALUATED.
*C,K,CK, and X are homeopathic dilutions: see BoironUSA.com/info for details.

INACTIVE INGREDIENT

Hard fat

QUESTIONS

1-800-BOIRON-1 (1-800-264-7661),
BoironUSA.com Info@boiron.com
Distributed by Boiron, Inc. Newtown Square, PA 19073